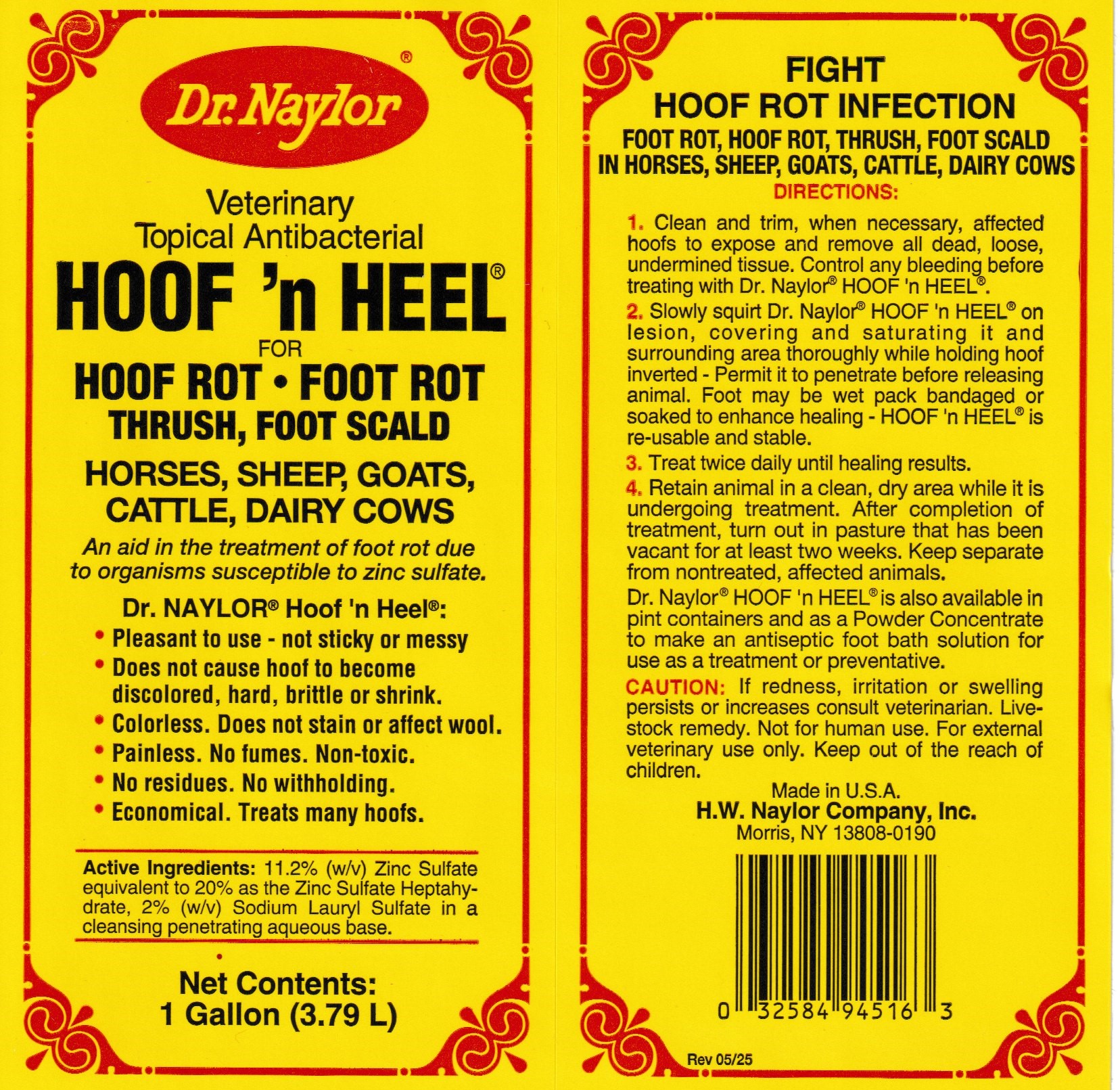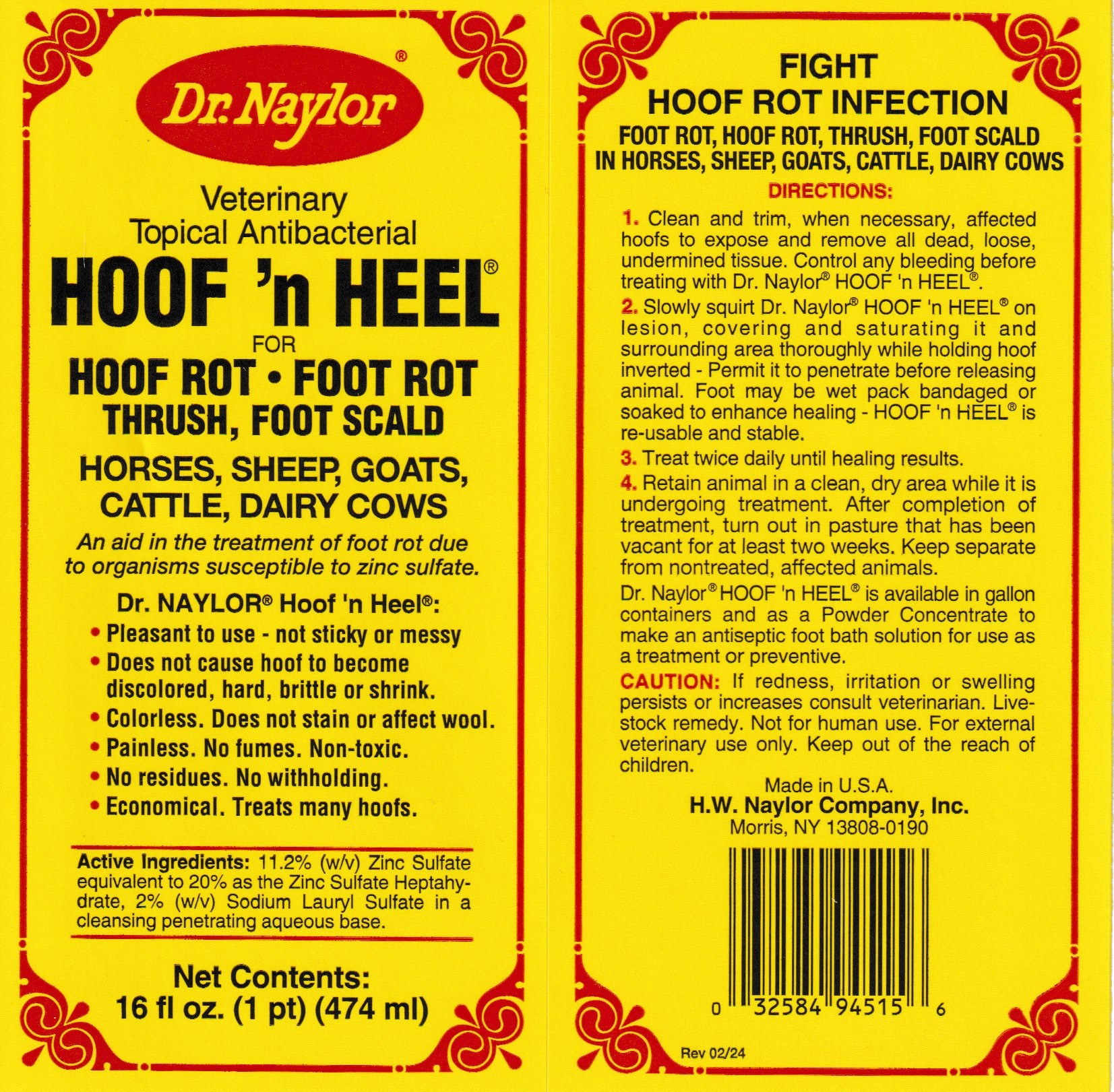 DRUG LABEL: HOOF n HEEL 
NDC: 15878-214 | Form: LIQUID
Manufacturer: H. W. Naylor Company Inc.
Category: animal | Type: OTC ANIMAL DRUG LABEL
Date: 20251210

ACTIVE INGREDIENTS: Zinc Sulfate 100 g/1000 mL; Sodium Lauryl Sulfate 18 g/1000 mL
INACTIVE INGREDIENTS: Water

HOOF 'n HEEL®

Active Ingredients

11.2% (w/v) Zinc Sulfate equivalent to 20% as the Zinc Sulfate Heptahydrate, 2% (w/v) Sodium Lauryl Sulfate in a cleansing penetrating aqueous base.

Purpose

An aid in the treatment of foot rot due to organisms susceptible to zinc sulfate.

Directions

1. Clean and trim, when necessary, affected hoofs to expose and remove all dead, loose, undermined tissue. Control any bleeding before treating with Dr. Naylor® HOOF 'n HEEL®.
2. Slowly squirt Dr. Naylor® HOOF 'n HEEL® on lesion, covering and saturating it and surrounding area thoroughly while holding hoof inverted - Permit it to penetrate before releasing animal. Foot may be wet pack bandaged or soaked to enhance healing - HOOF'n HEEL® is re-usable and stable.
3. Treat twice daily until healing results.
4. Retain animal in a clean, dry area while it is undergoing treatment. After completion of treatment, turn out in pasture that has been vacant for at least two weeks. Keep separate from nontreated, affected animals.

Safety

CAUTION: lf redness, irritation or swelling persists or increases consult veterinarian.

Livestock remedy. Not for human use.

For external veterinary use only.

Keep out of the reach of children.

Principal Display Panel - 16 ounce bottle

Dr. Naylor®
Veterinary Topical Antibacterial
HOOF 'n HEEL®
FOR

HOOF ROT ● FOOT ROT
THRUSH, FOOT SCALD
HORSES, SHEEP, GOATS, CATTLE, DAIRY COWS
An aid in the treatment of foot rot due to organisms susceptible to zinc sulfate.
Dr. NAYLOR® Hoof 'n Heel®:
• Pleasant to use - not sticky or messy
• Does not cause hoof to become discolored, hard, brittle or shrink.
• Colorless. Does not stain or affect wool.
• Painless. No fumes. Non-toxic.
• No residues. No withholding.
• Economical. Treats many hoofs.
Net Contents:
16 fl oz. (1 pt) (474 ml)
FIGHT HOOF ROT INFECTION
FOOT ROT, HOOF ROT, THRUSH, FOOT SCALD
IN HORSES, SHEEP, GOATS, CATTLE, DAIRY COWS

Made in U.S.A.

H.W. Naylor Company, Inc.

Morris NY 13808-0190

PRINCIPAL DISPLAY PANEL - 1 Gallon Bottle

Veterinary Topical Antibacterial

HOOF 'n HEEL®

FOR

HOOF ROT ● FOOT ROT
THRUSH, FOOT SCALD
HORSES, SHEEP, GOATS, CATTLE, DAIRY COWS

An aid in the treatment of foot rot due to organisms susceptible to zinc sulfate.

Dr. NAYLOR® Hoof 'n Heel®:
• Pleasant to use - not sticky or messy
• Does not cause hoof to become discolored, hard, brittle or shrink.
• Colorless. Does not stain or affect wool.
• Painless. No fumes. Non-toxic.
• No residues. No withholding.
• Economical. Treats many hoofs.

Net Contents:
1 Gallon (3.79 L)

FIGHT HOOF ROT INFECTION
FOOT ROT, HOOF ROT, THRUSH, FOOT SCALD
IN HORSES, SHEEP, GOATS, CATTLE, DAIRY COWS

Made in U.S.A.

H.W. Naylor Company, Inc.

Morris NY 13808-0190